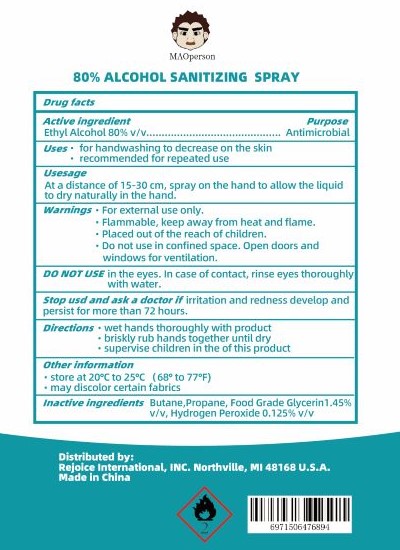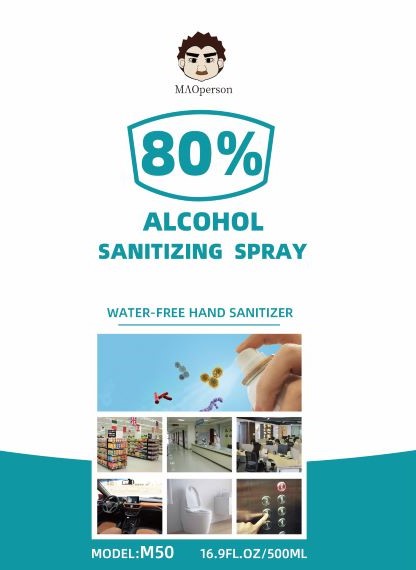 DRUG LABEL: SanitizingSpray
NDC: 71712-004 | Form: SPRAY
Manufacturer: Wuxi Huoban Daily-Use Chemicals Science and Technology Co., Ltd
Category: otc | Type: HUMAN OTC DRUG LABEL
Date: 20200720

ACTIVE INGREDIENTS: ALCOHOL 80 mL/100 mL
INACTIVE INGREDIENTS: GLYCERIN; HYDROGEN PEROXIDE; WATER; BUTANE; PROPANE

Active Ingredient(s)

Ethyl Alcohol 80% v/v.

Purpose

Antimicrobial

Use

- for handwashing to decrease on the skin
- recommended for repeated use

Warnings

For external use only. Flammable. Keep away from heat or flame

- Do not use in confined space. Open doors and windows for ventilation.

When using this product keep out of eyes, ears, and mouth. In case of contact with eyes, rinse eyes thoroughly with water.
Stop use and ask a doctor if irritation or rash occurs. These may be signs of a serious condition.
Keep out of reach of children. If swallowed, get medical help or contact a Poison Control Center right away.

Stop use and ask a doctor if irritation or rash occurs. These may be signs of a serious condition.

KEEP OUT OF REACH OF CHILDREN

Placed out of reach of children. If swallowed, get medical help or contact a Poison Control Center right away.

Directions

- Place enough product on hands to cover all surfaces. Rub hands together until dry.
- Supervise children under 6 years of age when using this product to avoid swallowing.

Other information

- Store between 20-25C (59-86F)
- may discolor certain fabrics

Inactive ingredients

butane, propane, food grade glycerin 1.45%, hydrogen peroxide 0.125% v/v